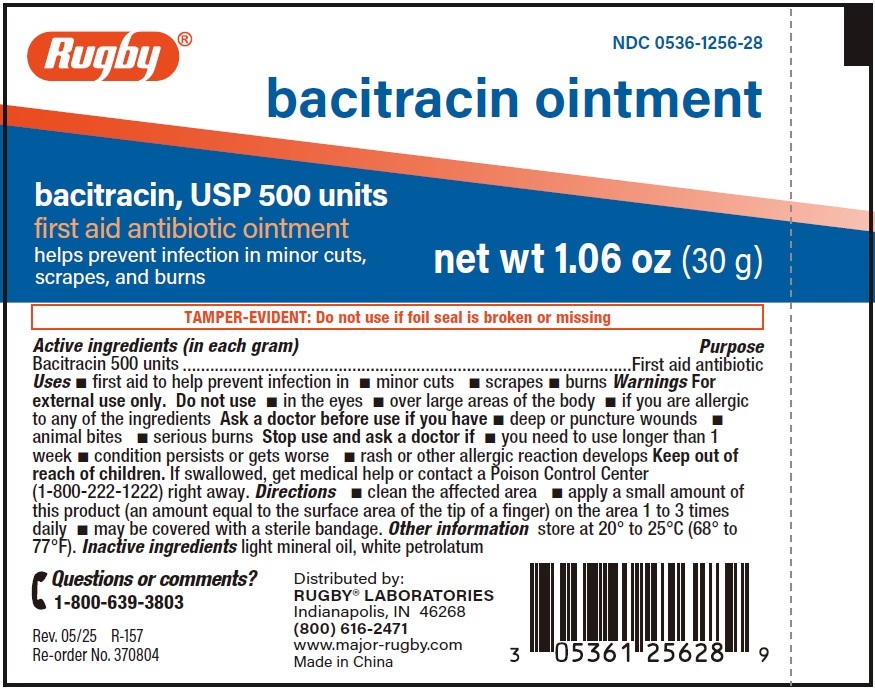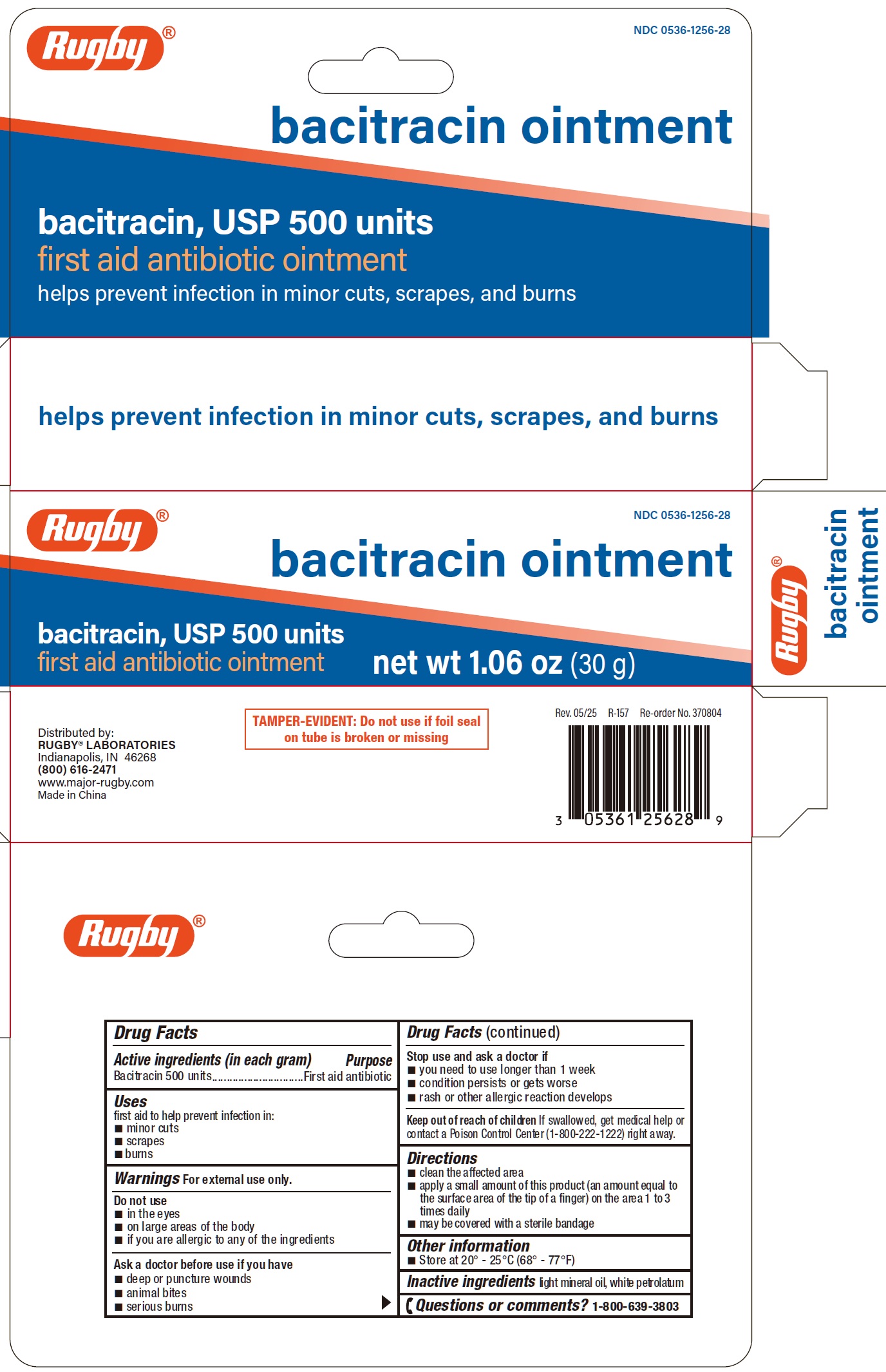 DRUG LABEL: Bacitracin
NDC: 0536-1256 | Form: OINTMENT
Manufacturer: RUGBY LABORATORIES
Category: otc | Type: HUMAN OTC DRUG LABEL
Date: 20250627

ACTIVE INGREDIENTS: BACITRACIN 500 U/1 g
INACTIVE INGREDIENTS: LIGHT MINERAL OIL; PETROLATUM

Bacitracin Ointment

Active ingredients (in each gram)

Bacitracin 500 units

Purpose

First aid antibiotic

Uses

first aid to help prevent infection in:

- minor cuts
- scrapes
- burns

Warnings

For external use only.

Do not use

- in the eyes
- on large areas of the body
- if you are allergic to any of the ingredients

Ask a doctor before use if you have

- deep or puncture wounds
- animal bites
- serious burns

Stop use and ask a doctor if

- you need to use longer than 1 week
- condition persists or gets worse
- rash or other allergic reaction develops

Keep out of reach of children

If swallowed, get medical help or contact a Poison Control Center(1-800-222-1222) right away.

Directions

- clean the affected area
- apply a small amount of this product (an amount equal to the surface area of the tip of a finger) on the area 1 to 3 times daily
- may be covered with a sterile bandage

Other information

- Store at 20° - 25°C (68° - 77°F)

Inactive ingredients

light mineral oil, white petrolatum

Questions or comments?

1-800-639-3803